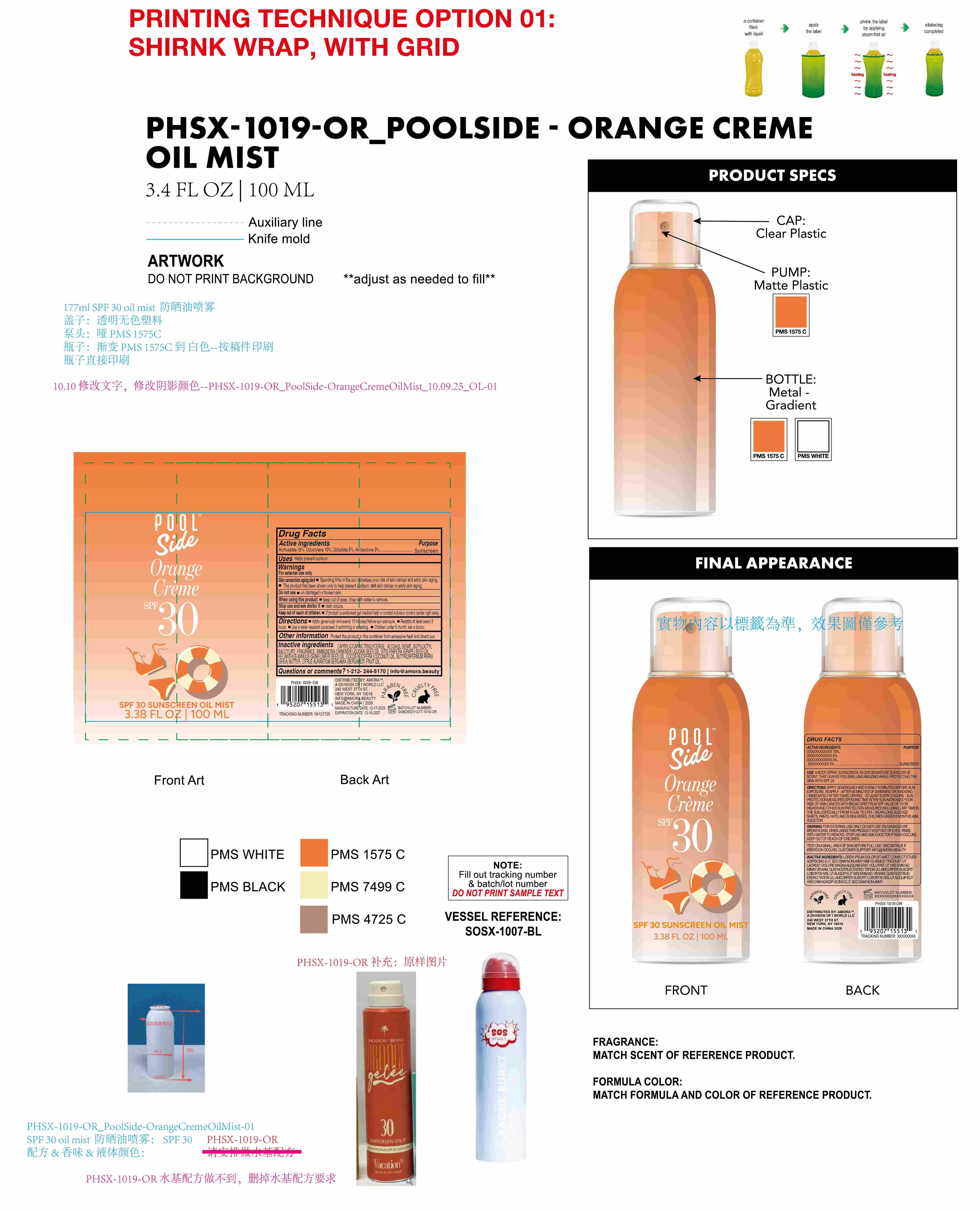 DRUG LABEL: Poolside Orange Creme SPF 30 Sunscreen oil mist
NDC: 85161-144 | Form: SPRAY
Manufacturer: Longway Technology(Guangzhou)Co.,Ltd.
Category: otc | Type: HUMAN OTC DRUG LABEL
Date: 20251203

ACTIVE INGREDIENTS: HOMOSALATE 0.15 g/1 mL; AVOBENZONE 0.03 g/1 mL; OCTISALATE 0.05 g/1 mL; OCTOCRYLENE 0.1 g/1 mL
INACTIVE INGREDIENTS: CAPRYLIC/CAPRIC TRIGLYCERIDE; HELIANTHUS ANNUUS (SUNFLOWER) SEED OIL; BUTYROSPERMUM PARKII (SHEA) BUTTER; FRAGRANCE 13576; BUTYLOCTYL SALICYLATE; ALCOHOL; CITRUS AURANTIUM BERGAMIA (BERGAMOT) FRUIT OIL; SIMMONDSIA CHINENSIS (JOJOBA) SEED OIL; COCOS NUCIFERA (COCONUT) OIL; VITIS VINIFERA (GRAPE) SEED OIL

ACTIVE INGREDIENT

Homosalate 15%, Octocrylene 10%, Octisalate 5%, Avobenzone 3%

QUESTIONS

1-212-244-5170 l info@amora.beauty

KEEP OUT OF REACH OF CHILDREN

If product is swallowed get medical help or contact a poison control center right away.

PURPOSE

Sunscreen

OTHER SAFETY INFORMATION

Protect the product in this container from excessive heat and direct sun.

INACTIVE INGREDIENT

CAPRYLIC/CAPRIC TRIGLYCERIDE, ALCOHOL DENAT., BUTYLOCTYL SALICYLATE, FRAGRANCE, SIMMONDSIA CHINENSIS (JOJOBA) SEED OIL, VITIS VINIFERA (GRAPE) SEED OIL, HELIANTHUS ANNUUS (SUNFLOWER) SEED OIL, COCOS NUCIFERA (COCONUT) OIL, BUTYROSPERMUM PARKII (SHEA) BUTTER, CITRUS AURANTIUM BERGAMIA (BERGAMOT) FRUIT OIL

Warnings

For external use only.
Skin cancer/skin aging alert

Spending time in the sun increases your risk of skin cancer and early skin aging.

This product has been shown only to help prevent sunbur, not skin cancer or early skin aging.

Do not use on damaged or broken skin.
When using this product keep out of eyes. rinse with water to remove.
Stop use and ask doctor if rash occurs.
Keep out of reach of chlldren. If product is swallowed get medical help or contact a poison control center right away.

Directions .

Apply generously and evenly 15 minutes before sun exposure.

Reapply at least every 2 hours.

Use a water resistant sunscreen if swimming or sweating.

Chlldren under 6 month: ask a doctor.

INDICATIONS AND USAGE

For external use only.